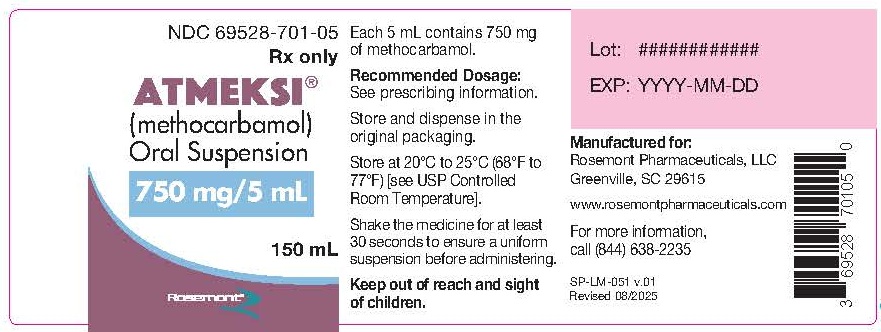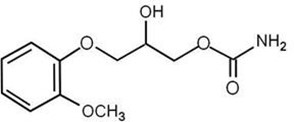 DRUG LABEL: ATMEKSI
NDC: 69528-701 | Form: SUSPENSION
Manufacturer: Metacel Pharmaceuticals, LLC
Category: prescription | Type: HUMAN PRESCRIPTION DRUG LABEL
Date: 20251121

ACTIVE INGREDIENTS: METHOCARBAMOL 750 mg/5 mL
INACTIVE INGREDIENTS: CITRIC ACID MONOHYDRATE; SODIUM CITRATE; MAGNESIUM ALUMINUM SILICATE; SODIUM BENZOATE; GLYCERIN; SUCRALOSE; CARBOXYMETHYLCELLULOSE SODIUM; WATER

HIGHLIGHTS OF PRESCRIBING INFORMATION

These highlights do not include all the information needed to use ATMEKSI® (methocarbamol) oral suspension safely and effectively. See full prescribing information for ATMEKSI (methocarbamol) oral suspension.
ATMEKSI (methocarbamol) oral suspension
Initial U.S. Approval: 05/07/2018

1 INDICATIONS AND USAGE

ATMEKSI (methocarbamol) oral suspensionis a muscle relaxant indicated as:

- an adjunct to rest, physical therapy, and other measures for the relief of discomfort associated with acute, painful musculoskeletal conditions in patients 16 and older.

2 DOSAGE AND ADMINISTRATION

- Adults

Initial dosage: 1,500 mg (10 mL) 4 times daily

Maintenance dosage: 750 mg (5 mL) every 4 hours or 1,500 mg (10 mL) 3 times daily

Six grams a day are recommended for the first 48 to 72 hours of treatment. (For severe conditions 8 grams a day may be administered). Thereafter, the dosage can usually be reduced to approximately 4 grams a day.

3 DOSAGE FORMS AND STRENGTHS

- oral suspension: 750 mg/5 mL

4.1 Hypersensitivity

Hypersensitivity to ATMEKSI or any component in the product (4.1)

5 WARNINGS AND PRECAUTIONS

- ATMEKSI may potentiate the effects of CNS (central nervous system) depressants and alcohol (5.1)
- ATMEKSI may impair mental and/or physical abilities required for performance of hazardous tasks, such as operating machinery or driving a motor vehicle (5.2)

6 ADVERSE REACTIONS

- Body:Anaphylactic reaction, angioneurotic edema, fever, headache (6)
- Cardiovascular system:Bradycardia, flushing, hypotension, syncope, thrombophlebitis (6)
- Digestive system:Dyspepsia, jaundice (including cholestatic jaundice), nausea and vomiting (6)
- Hemic and lymphatic system:Leukopenia (6)
- Immune system:Hypersensitivity reactions (6)
- Nervous system:Amnesia, confusion, diplopia, dizziness or lightheadedness, drowsiness, insomnia, mild muscular incoordination, nystagmus, sedation, seizures (including grand mal), vertigo (6)
- Skin and special senses:Blurred vision, conjunctivitis, nasal congestion, metallic taste, pruritus, rash and urticaria (6)

To report SUSPECTED ADVERSE REACTIONS, contact Rosemont Pharmaceuticals, LLC. at 1-844-638-2235 or FDA at 1-800-FDA-1088 orwww.fda.gov/medwatch .

7 DRUG INTERACTIONS

- ATMEKSI may inhibit the effect of pyridostigmine bromide. Patients with myasthenia gravis should be monitored closely for symptoms of myasthenia gravis such as weakness. If symptoms of myasthenia gravis are observed, treatment with ATMEKSI should be stopped immediately (7.2)
- Laboratory test interference: Methocarbamol may cause color interference in the following screening tests: 5-hydroxyindoleacetic acid (using nitrosonaphthol reagent) and VMA (Giltow method) (7.3)

8 USE IN SPECIFIC POPULATIONS

Lactation: The developmental and health benefits of breastfeeding should be considered along with the mother’s clinical need for ATMEKSI and any potential adverse effects on the breastfed infant from methocarbamol or the underlying maternal condition .

FULL PRESCRIBING INFORMATION

1 INDICATIONS AND USAGE

1.1 Acute, painful musculoskeletal conditions.

ATMEKSI is indicated as an adjunct to rest, physical therapy, and other measures for the relief of discomfort associated with acute, painful musculoskeletal conditions in patients 16 and older.

2 DOSAGE AND ADMINISTRATION

2.1 Important Dosage and Administration Instructions

Initial dosage: 1,500 mg (10 mL) 4 times daily

Maintenance dosage: 750 mg (5 mL) every 4 hours or 1,500 mg (10 mL) 3 times daily

Six grams a day are recommended for the first 48 to 72 hours of treatment. (For severe conditions 8 grams a day may be administered). Thereafter, the dosage can usually be reduced to approximately 4 grams a day.

Inform the patient to shake the drug product for at least 30 seconds to ensure it is uniform before administration.

3 DOSAGE FORMS AND STRENGTHS

Oral Suspension: 750 mg/5 mL of methocarbamol as a white to off-white suspension with a fruit flavor

4 CONTRAINDICATIONS

4.1 Hypersensitivity

ATMEKSI is contraindicated in patients hypersensitive to methocarbamol or to any of the oral suspension components.

5 WARNINGS AND PRECAUTIONS

5.1 CNS Depressants and Alcohol Use

ATMEKSI may potentiate the effects of CNS (central nervous system) depressants and alcohol. Patients receiving ATMEKSI (methocarbamol) Oral Suspension should be cautioned about combined effects with alcohol and other CNS depressants [ see Drug Interactions (7.1)].

5.2 Use in Activities Requiring Mental Alertness

ATMEKSI may impair mental and/or physical abilities required for performance of hazardous tasks, such as operating machinery or driving a motor vehicle. Patients should be cautioned about operating machinery, including automobiles, until they are reasonably certain that methocarbamol therapy does not adversely affect their ability to engage in such activities.

6 ADVERSE REACTIONS

The following serious adverse reaction is described elsewhere in the labeling:

- Interactions with CNS Depressants and Alcohol [ see Warnings and Precautions (5.1)]

The following adverse reactions associated with the use of methocarbamol have been identified in clinical studies or postmarketing reports. Because some of these reactions were reported voluntarily from a population of uncertain size, it is not always possible to reliably estimate their frequency or establish a causal relationship to drug exposure.

Adverse reactions reported with the administration of methocarbamol include:

Body as a whole: Anaphylactic reaction, angioneurotic edema, fever, headache.

Cardiovascular system:Bradycardia, flushing, hypotension, syncope, thrombophlebitis.

Digestive system:Dyspepsia, jaundice (including cholestatic jaundice), nausea and vomiting.

Hemic and lymphatic system:Leukopenia.

Immune System:Hypersensitivity reactions.

Nervous system:Amnesia, confusion, diplopia, dizziness or lightheadedness, drowsiness, insomnia, mild muscular incoordination, nystagmus, sedation, seizures (including grand mal), vertigo.

Skin and special senses:Blurred vision, conjunctivitis, nasal congestion, metallic taste, pruritus, rash, urticaria.

7 DRUG INTERACTIONS

7.1 CNS drugs and alcohol

ATMEKSI may potentiate the effects of CNS (central nervous system) depressants and alcohol [ see Warnings and Precautions (5.1)].

7.2 Pyridostigmine Bromide

ATMEKSI may inhibit the effect of pyridostigmine bromide. Patients with myasthenia gravis should be monitored closely for symptoms of myasthenia gravis such as weakness. If symptoms of myasthenia gravis are observed, treatment with ATMEKSI should be stopped immediately.

7.3 Drug/Laboratory Test Interactions

ATMEKSI may cause color interference in certain screening tests for 5-hydroxyindoleacetic acid (5-HIAA) using nitrosonaphthol reagent and in screening tests for urinary vanillylmandelic acid (VMA) using the Gitlow method.

8 USE IN SPECIFIC POPULATIONS

8.1 Pregnancy

Risk Summary

Limited data from case reports over decades of use with methocarbamol during pregnancy have not identified an increased risk of major birth defects, miscarriage or other adverse maternal or fetal outcomes.

The background risk of major birth defects and miscarriage for the indicated population is unknown. All pregnancies have a background risk of birth defect, loss, or other adverse outcomes. In the U.S. general population, the estimated background risk of major birth defects and miscarriage in clinically recognized patients is 2 to 4% and 15 to 20% respectively.

8.2 Lactation

Risk Summary

There are no data on the presence of methocarbamol or its metabolites in human milk, the effects on a breastfed infant or the effects on milk production. Methocarbamol and/or its metabolite are present in animal milk. When a drug is present in animal milk, it is likely that the drug will be present in human milk. The developmental and health benefits of breastfeeding should be considered along with the mother’s clinical need for ATMEKSI and any potential adverse effects on the breastfed infant from ATMEKSI or the underlying maternal condition.

8.4 Pediatric Use

Safety and effectiveness of methocarbamol oral suspension in pediatric patients below the age of 16 have not been established.

10 OVERDOSAGE

Clinical Presentation

Deaths have been reported with an overdose of methocarbamol alone and when methocarbamol was used with other CNS depressants, including alcohol. Limited information is available on the acute toxicity of methocarbamol. Symptoms of overdose include the following: respiratory depression, nausea, drowsiness, blurred vision, hypotension, seizures, coma, and death. Other CNS depressants (e.g., benzodiazepines, opioids, tricyclic antidepressants) can have an additive effect, even when taken at recommended dosages.

Treatment of Overdose

The standard of treatment is supportive care, including monitoring for CNS and respiratory depression and managing airway as needed, monitoring urinary output and vital signs, and administration of intravenous fluids if necessary.

Hypotension should be treated with intravenous fluids and vasopressors as needed. Gastrointestinal decontamination procedures (including emesis) should generally be avoided because aspiration may result from CNS depression and seizures. Extracorporeal elimination such as hemodialysis or plasmapheresis has no proven clinical benefit. Consider contacting the Poison Help line (1-800-222-1222) or a medical toxicologist for additional overdose management recommendations.

11 DESCRIPTION

ATMEKSI (methocarbamol) Oral Suspension is a central nervous system (CNS) depressant with sedative and musculoskeletal relaxant properties.

The chemical name of methocarbamol is (±)1,2-Propanediol, 3-(2-methoxyphenoxy)-, 1-carbamate, or (±)-3-(o-Methoxyphenoxy)-1,2-propanediol 1-carbamate and has the empirical formula C11H15NO5. Its molecular weight is 241.24g/mol. The structural formula is shown below:

Methocarbamol is a white powder, sparingly soluble in water and in chloroform, soluble in alcohol (only with heating), insoluble in benzene and in n-hexane.

ATMEKSI (methocarbamol) Oral Suspension is a white to off-white suspension with a fruit flavor and a pH range of 3.2 – 4.8.

ATMEKSI (methocarbamol) Oral Suspension contains the following inactive ingredients: citric acid monohydrate, glycerin, magnesium aluminum silicate, purified water, sodium benzoate, sodium carboxymethylcellulose, sodium citrate, sucralose and fruit flavor.

12 CLINICAL PHARMACOLOGY

12.1 Mechanism of Action

The mechanism of action of methocarbamol in humans has not been established but may be due to general central nervous system (CNS) depression. It has no direct action on the contractile mechanism of striated muscle, the motor end plate, or the nerve fiber.

12.3 Pharmacokinetics

Absorption

After oral administration in healthy volunteers, ATMEKSI is rapidly absorbed with a median Tmax of 0.66 hours. Food decreases the extent and delays the rate of absorption of methocarbamol. In the presence of food, the Cmax is decreased by 51% and the AUC is decreased by 31%. The median Tmax is delayed to 1.6 hours.

Distribution

Methocarbamol demonstrates moderate binding to plasma proteins, typically ranging from 46% to 50%.

Elimination

In healthy volunteers, the plasma clearance of methocarbamol ranges between 0.20 and 0.80 L/h/kg. The mean plasma elimination half-life of ATMEKSI in healthy volunteers is approximately 1.3 hours and 1.5 hours when administered with or without food.

Metabolism

Methocarbamol is metabolized via dealkylation and hydroxylation. Conjugation of methocarbamol also is likely. Essentially all methocarbamol metabolites are eliminated in the urine.

Excretion

Small amounts of unchanged methocarbamol also are excreted in the urine.

Specific Populations

Geriatric Patients

The mean (± SD) elimination half-life of methocarbamol in elderly healthy volunteers (mean (± SD) age, 69 (± 4) years) was slightly prolonged compared to a younger (mean (± SD) age, 53.3 (± 8.8) years), healthy population (1.5 (± 0.4) hours versus 1.1 (± 0.27) hours, respectively). The fraction of bound methocarbamol was slightly decreased in the elderly versus younger volunteers (41 to 43% versus 46 to 50%, respectively).

Pediatric Patients

Safety and effectiveness of methocarbamol oral suspension in pediatric patients below the age of 16 have not been established.

Patients with Renal Impairment

The clearance of methocarbamol in 8 renally-impaired patients on maintenance hemodialysis was reduced about 40% compared to 17 normal subjects, although the mean (± SD) elimination half-life in these two groups was similar: 1.2 (± 0.6) versus 1.1 (± 0.3) hours, respectively.

Patients with Hepatic Impairment

In 8 patients with cirrhosis secondary to alcohol abuse, the mean total clearance of methocarbamol was reduced approximately 70% compared to that obtained in 8 age- and weight-matched normal subjects. The mean (± SD) elimination half-life in the cirrhotic patients and the normal subjects was 3.38 (± 1.62) hours and 1.11 (± 0.27) hours, respectively. The percent of methocarbamol bound to plasma proteins was decreased to approximately 40 to 45% compared to 46 to 50% in the normal subjects.

13 NONCLINICAL TOXICOLOGY

13.1 Carcinogenesis, Mutagenesis, Impairment of Fertility

Carcinogenesis

Long-term studies to evaluate the carcinogenic potential of methocarbamol have not been performed.

Mutagenesis

No studies have been conducted to assess the effect of methocarbamol on mutagenesis.

Impairment of Fertility

No studies have been conducted to assess the effect of methocarbamol on its potential to impair fertility.

16 HOW SUPPLIED/STORAGE AND HANDLING

16.1 How Supplied

ATMEKSI (methocarbamol) Oral Suspension contains 750 mg/5 mL methocarbamol. It is a white to off-white suspension with a fruit flavor and is supplied in bottles of 150 mL with a child-resistant closure (NDC 69528-701-05).

16.2 Storage and Handling

Store at 20°C to 25°C (68°F to 77°F) [see USP Controlled Room Temperature]. Keep out of reach and sight of children.

17 PATIENT COUNSELING INFORMATION

- Caution patients that ATMEKSI may cause drowsiness or dizziness, which may impair their ability to operate motor vehicles or machinery.
- Because ATMEKSI may possess a general CNS-depressant effect, caution patients about combined effects with alcohol and other CNS depressants.

Manufactured for:

Rosemont Pharmaceuticals, LLC

Greenville, SC 29615

www.rosemontpharmaceuticals.com

ATMEKSI®is a registered trademark of Rosemont Pharmaceuticals Ltd.

PI-MET-01-001

Principal Display Panel - 150 mL Bottle

NDC 69528-701-05

Atmeksi

(methocarbamol)

Oral Suspension

750 mg/5 mL

150 mL